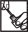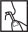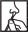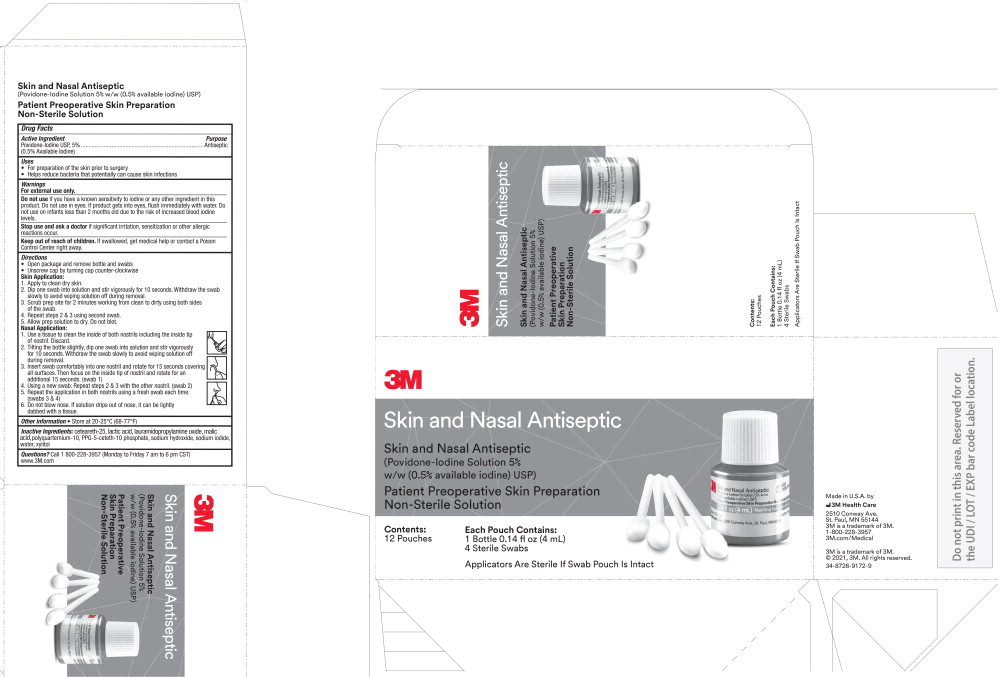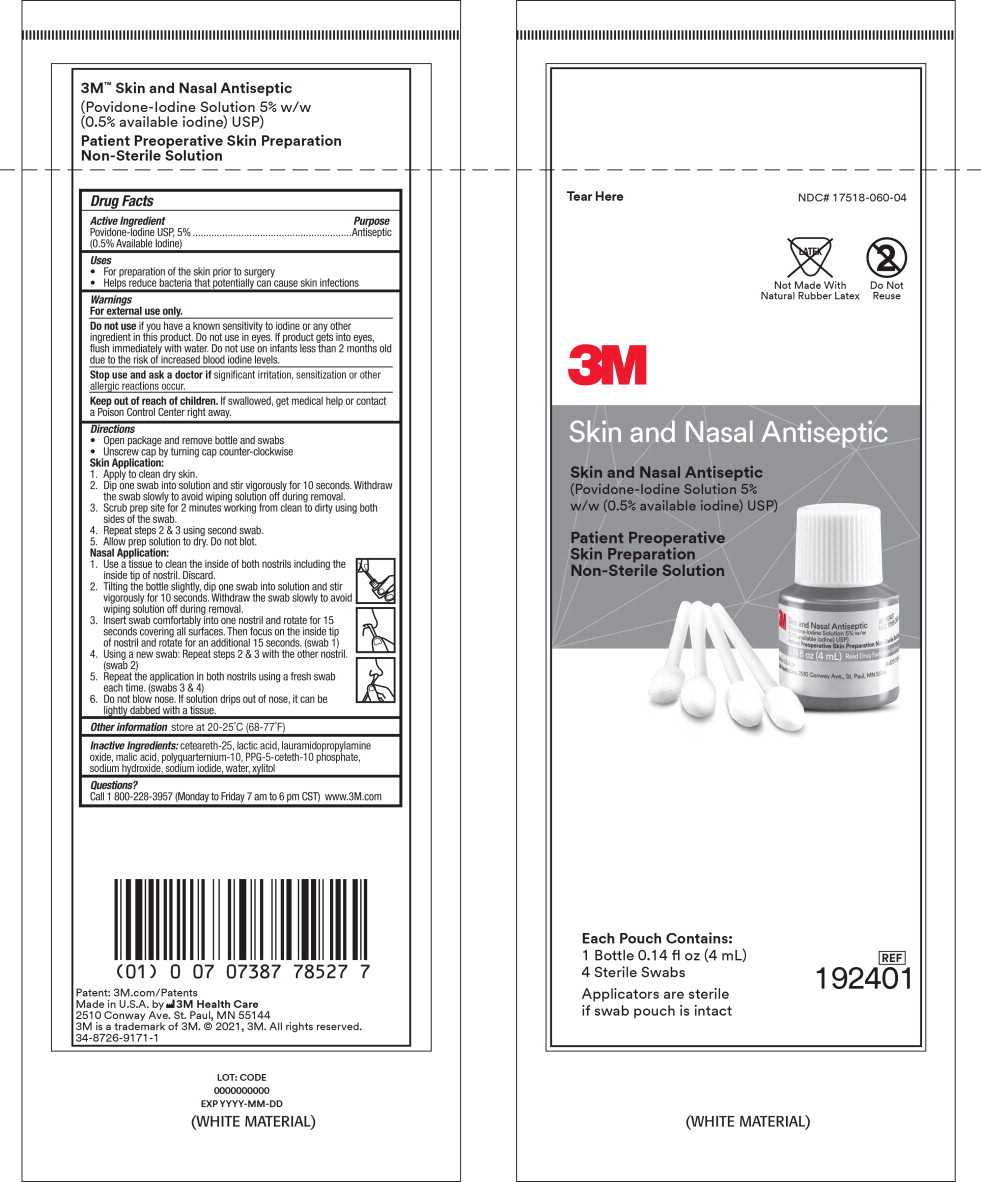 DRUG LABEL: 3M Skin and Nasal Antiseptic
NDC: 17518-060 | Form: SOLUTION
Manufacturer: Solventum US LLC
Category: otc | Type: HUMAN OTC DRUG LABEL
Date: 20240801

ACTIVE INGREDIENTS: Povidone-Iodine 5 mg/1 mL
INACTIVE INGREDIENTS: Lactic Acid; Malic Acid; Sodium Hydroxide; Sodium Iodide; ceteareth-25; Water; Xylitol; Lauramidopropylamine Oxide

3M™ Skin and Nasal Antiseptic
(Povidone-Iodine Solution 5% w/w (0.5% available iodine) USP)
Patient Preoperative Skin Preparation

Drug Facts

Active Ingredient

Povidone-Iodine USP, 5%
(0.5% Available Iodine)

Purpose

Antiseptic

Uses

- For preparation of the skin prior to surgery
- Helps reduce bacteria that potentially can cause skin infections

Warnings

For external use only.

Do not use if you have a known sensitivity to iodine or any other ingredient in this product. Do not use in eyes. If product gets into eyes, flush immediately with water. Do not use on infants less than 2 months old due to the risk of increased blood iodine levels.

Stop use and ask a doctor if significant irritation, sensitization or other allergic reactions occur.

Keep out of reach of children. If swallowed, get medical help or contact a Poison Control Center right away.

Directions

- Open package and remove bottle and swabs
- Unscrew cap by turning cap counter-clockwise

Skin Application:

1. Apply to clean dry skin.
2. Dip one swab into solution and stir vigorously for 10 seconds. Withdraw the swab slowly to avoid wiping solution off during removal.
3. Scrub prep site for 2 minutes working from clean to dirty using both sides of the swab.
4. Repeat steps 2 & 3 using second swab.
5. Allow prep solution to dry. Do not blot.

Nasal Application:

1. Use a tissue to clean the inside of both nostrils including the inside tip of nostril. Discard.
2. Tilting the bottle slightly, dip one swab into solution and stir vigorously for 10 seconds. Withdraw the swab slowly to avoid wiping solution off during removal.
3. Insert swab comfortably into one nostril and rotate for 15 seconds covering all surfaces. Then focus on the inside tip of nostril and rotate for an additional 15 seconds. (swab 1)
4. Using a new swab: Repeat steps 2 & 3 with the other nostril. (swab 2)
5. Repeat the application in both nostrils using a fresh swab each time. (swabs 3 & 4)
6. Do not blow nose. If solution drips out of nose, it can be lightly dabbed with at tissue.

Other information

store at 20-25°C (68-77°F)

Inactive Ingredients:

ceteareth-25, lactic acid, lauramidopropylamine oxide, malic acid, polyquarternium-10, PPG-5-ceteth-10 phosphate, sodium hydroxide, sodium iodide, water, xylitol

Questions?

Call 1 800-228-3957 (Monday to Friday 7 am to 6 pm CST) www.3M.com

Principal Display Panel – Carton

3M Skin and Nasal Antiseptic

(Povidone-Iodine Solution 5% w/w (0.5% available iodine) USP)

Patient Preoperative Skin Preparation

Non-Sterile Solution

Contents:

12 pouches

Each Pouch Contains:

1 Bottle 0.14 fl oz (4 mL)

4 Sterile Swabs

Applicators Are Sterile If Swab Pouch Is Intact

Made in U.S.A. by

3M Health Care

2510 Conway Ave.

St. Paul, MN 55144

3M is a trademark of 3M

1-800-228-3957

3m.com/Medical

3M is a trademark of 3M

© 2021, 3M. All rights reserved.

34-8726-9172-9

Principal Display Panel – Pouch Label

NDC 17518-060-04

Not Made With Natural Rubber Latex

Do Not Reuse

3M Skin and Nasal Antiseptic

Skin and Nasal Antiseptic

(Povidone-Iodine Solution 5% w/w (0.5% available iodine) USP)

Patient Preoperative

Skin Preparation

Non-Sterile Solution

Each Pouch Contains:

1 Bottle 0.14 fl oz (4 mL)

4 Sterile Swabs

Applicators are sterile if swab pouch is intact

REF

192401